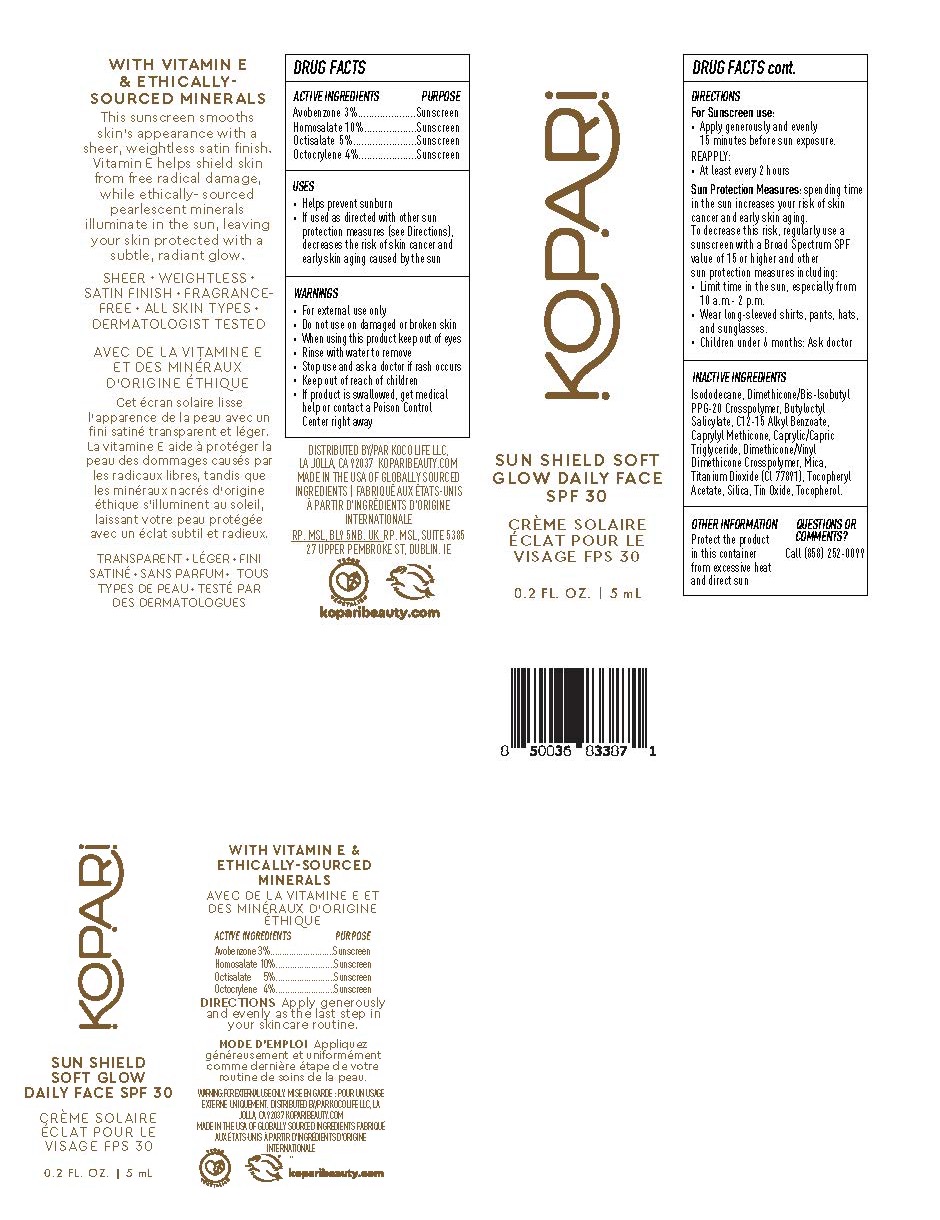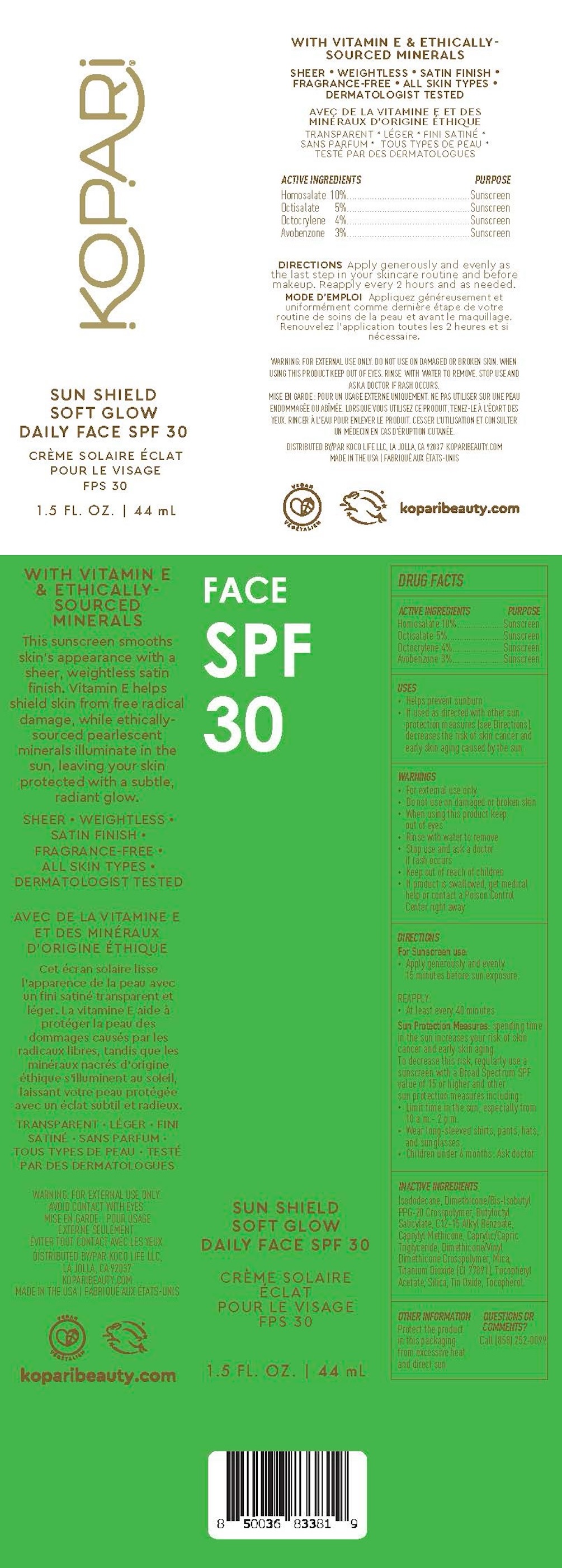 DRUG LABEL: Sun Shield Soft Glow Daily Face SPF30
NDC: 84130-006 | Form: CREAM
Manufacturer: Koco Life LLC
Category: otc | Type: HUMAN OTC DRUG LABEL
Date: 20240701

ACTIVE INGREDIENTS: AVOBENZONE 30 mg/1 mL; OCTISALATE 50 mg/1 mL; OCTOCRYLENE 40 mg/1 mL; HOMOSALATE 100 mg/1 mL
INACTIVE INGREDIENTS: ISODODECANE; ALKYL (C12-15) BENZOATE; TOCOPHEROL; MICA; BUTYLOCTYL SALICYLATE; DIMETHICONE/BIS-ISOBUTYL PPG-20 CROSSPOLYMER; SILICON DIOXIDE; STANNOUS OXIDE; TITANIUM DIOXIDE; .ALPHA.-TOCOPHEROL ACETATE; CAPRYLYL TRISILOXANE; MEDIUM-CHAIN TRIGLYCERIDES; DIMETHICONE/VINYL DIMETHICONE CROSSPOLYMER (HARD PARTICLE)

Sun Shield Soft Glow Daily Face SPF30

Active ingredients

Homosalate 10%

Octisalate 5%

Octocrylene 4%

Avobenzone 3%

Purpose

Homosalate 10%....................Sunscreen

Octisalate 5%........................Sunscreen

Octocrylene 4%......................Sunscreen

Avobenzone 3%......................Sunscreen

Uses

• Helps prevent sunburn

• If used as directed with other sunprotection measures (see Directions),decreases the risk of skin cancer andearly skin aging caused by the sun

Warnings

• For external use only

• Do not use on damaged or broken skin

• When using this product keepout of eyes

• Rinse with water to remove

• Stop use and ask a doctorif rash occurs

• Keep out of reach of children

• If product is swallowed, get medicalhelp or contact a Poison Control Center right away

Directions

For Sunscreen use:

• Apply generously and evenly 15 minutes before sun exposure.

REAPPLY:

• At least every 40 minutes

Sun Protection Measures: spending time in the sun increases your risk of skin cancer and early skin aging. To decrease this risk, regularly use a sunscreen with a Broad Spectrum SPF value of 15 or higher and other sun protection measures including:• Limit time in the sun, especially from 10 a.m.- 2 p.m.• Wear long-sleeved shirts, pants, hats,and sunglasses.• Children under 6 months: Ask doctor

Inactive ingredients

Isododecane, Dimethicone/Bis-lsobutyl PPG-20 Crosspolymer, Butyloctyl Salicylate, C12-15 Alkyl Benzoate, Caprylyl Methicone, Caprylic/Capric Triglyceride, Dimethicone/Vinyl Dimethicone Crosspolymer, Mica, Titanium Dioxide (Cl 77891), Tocopheryl Acetate, Silica, Tin Oxide, Tocopherol.

Other information

Protect the product in this packaging from excessive heat and direct sun

Questions or comments?

Call (858) 252-0099

PACKAGE LABEL

Kopari

Sun Shield

Soft Glow

Daily Face

SPF 30